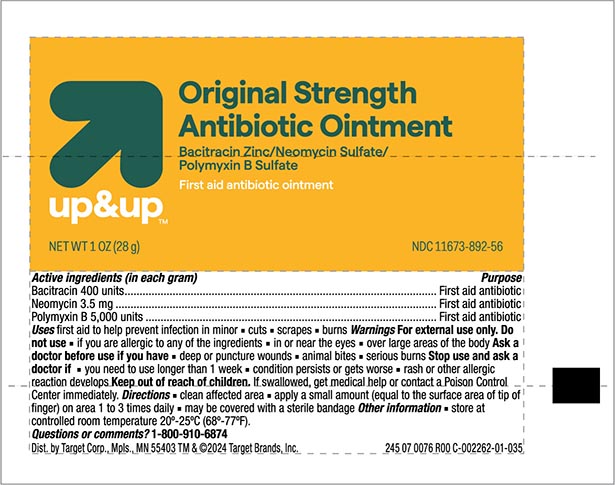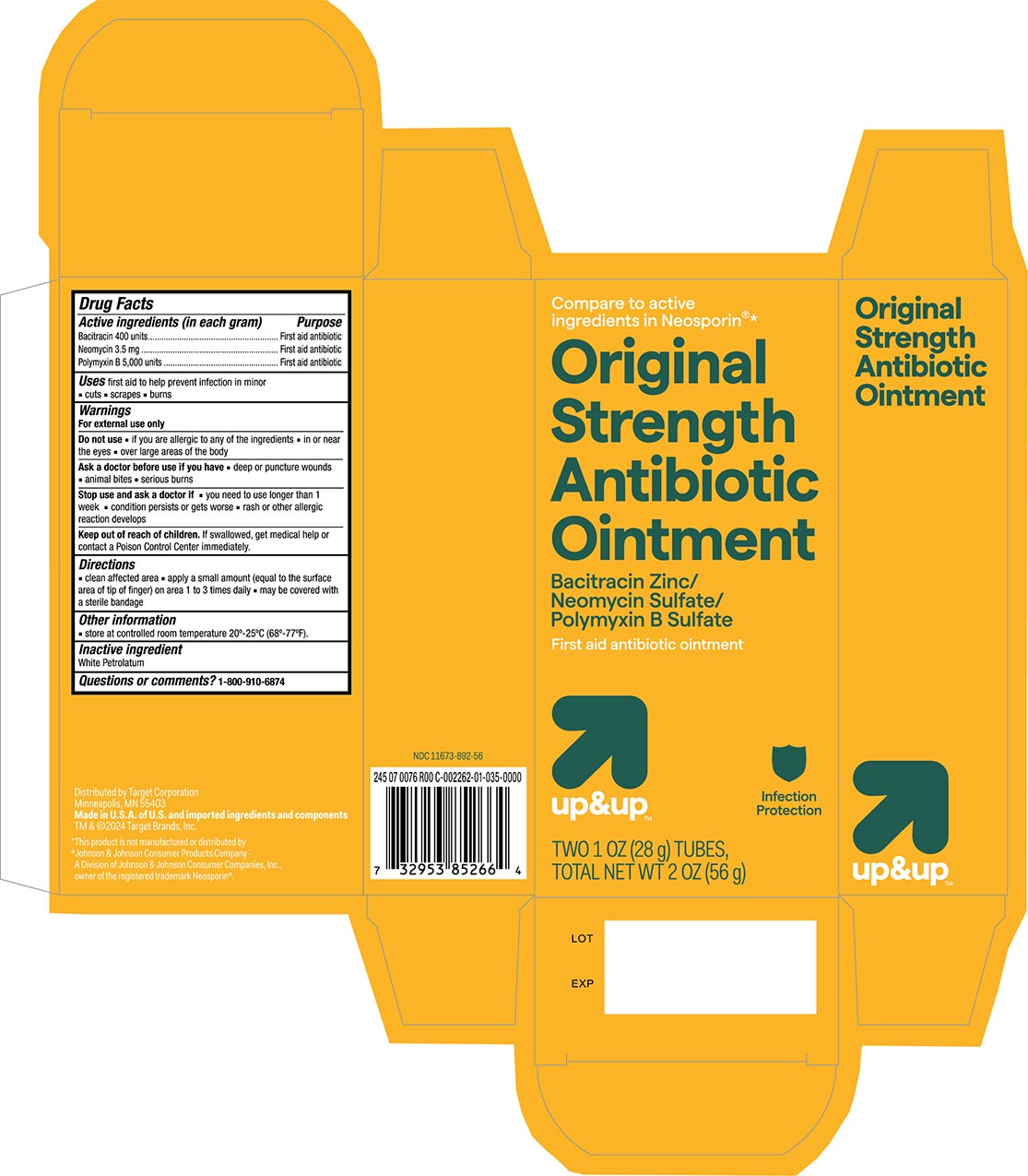 DRUG LABEL: Triple Antibiotic
NDC: 11673-892 | Form: OINTMENT
Manufacturer: Target Corporation
Category: otc | Type: HUMAN OTC DRUG LABEL
Date: 20240117

ACTIVE INGREDIENTS: BACITRACIN ZINC 400 [USP'U]/1 g; POLYMYXIN B SULFATE 5000 [USP'U]/1 g; NEOMYCIN SULFATE 3.5 mg/1 g
INACTIVE INGREDIENTS: PETROLATUM

Target Up &Up Triple Antibiotic Ointment

Active Ingredients

Bacitracin 400

Neomycin 3.5 mg

Polymyxin B 5,000 units

Purpose

First aid antibiotic

First aid antibiotic

First aid antibiotic

Uses

First aid to help prevent infection in minor:

- cuts
- scrapes
- burns

Warnings

For external use only

Do not use if

- in or near the eyes
- on large areas of the body

Ask a doctor before use if you have

- deep or puncture wounds
- animal bites
- serious burns

Stop use and ask a doctor if

- you need ot use longer than 1 week
- condition persists or gets worse
- a rash or other allergic reaction develops

KEEP OUT OF REACH OF CHILDREN

Keep out of the reach of children. If swallowed get medical help or contact a Poison Control Center immediately.

Directions

- clean the affected area
- apply a small amount (equal to surface area of tip of finger) on the area 1 to 3 times daily.
- may be covered with a sterile bandage

Other information

Store at a controlled room temperature 20º-25ºC (68º-77ºF)

Inactive ingredients

Petrolatum

Principal Display Panel

Target Up&Up NDC 11673-892-56

Tripel Anitibiotic Ointment

Polymxiin B Sulfate

Bacitracin Zinc

Neomycin Sulfate

First aid Antibiotic Ointment

NET WT 1oz(28g)

Total NET WT 2OZ (56g)